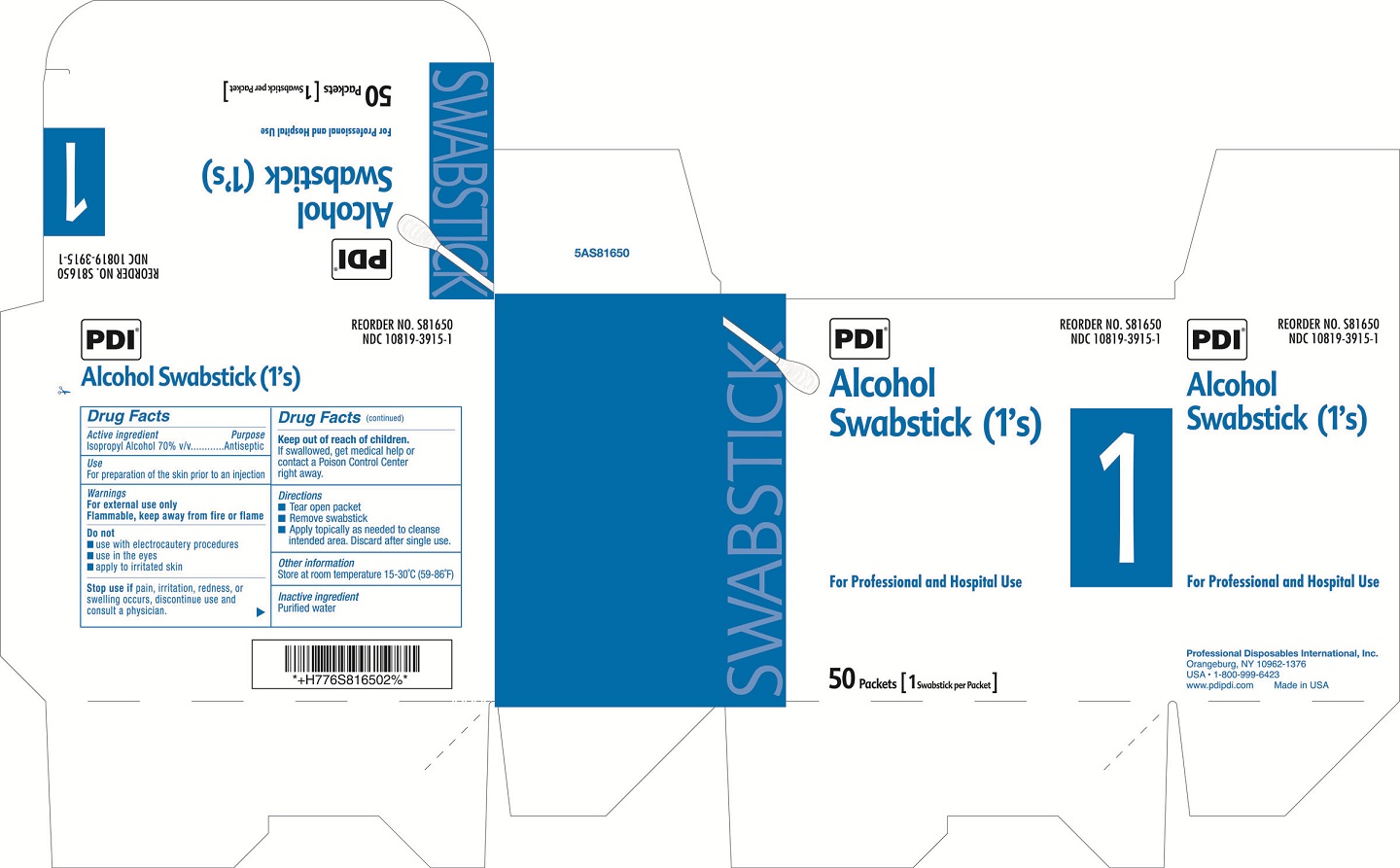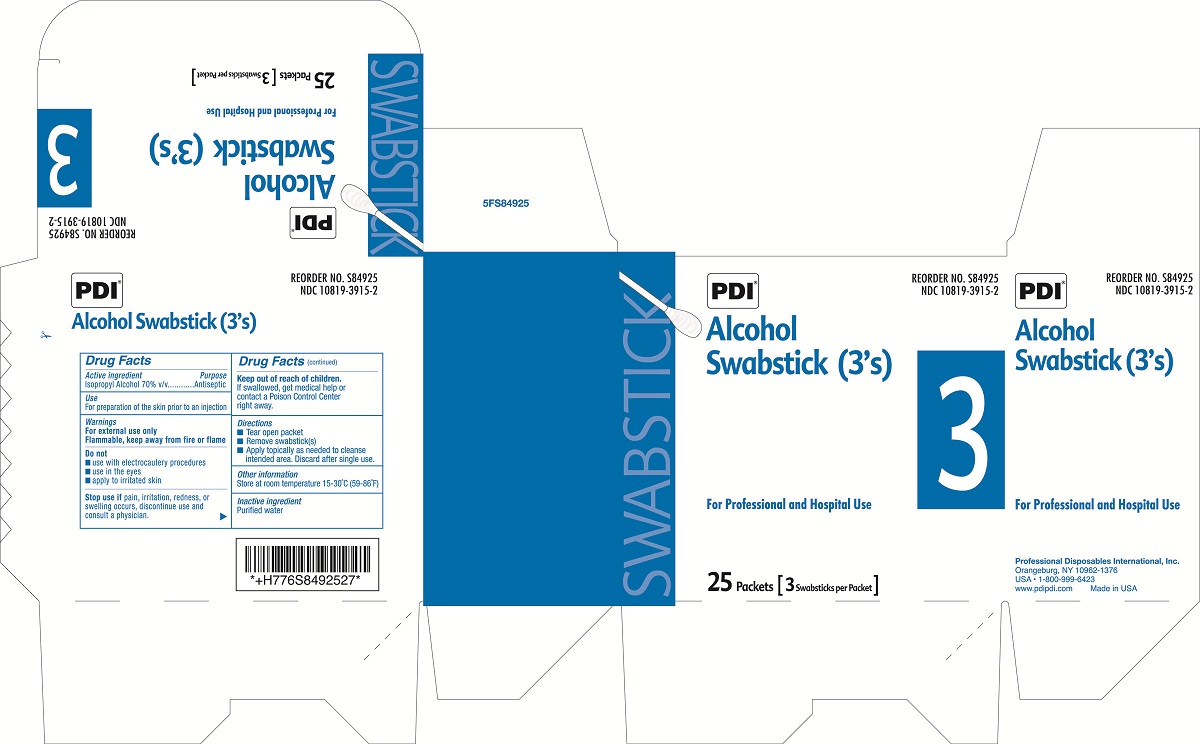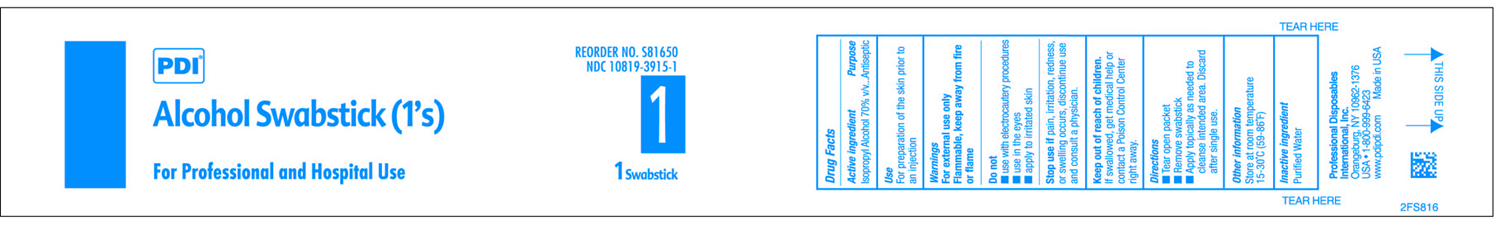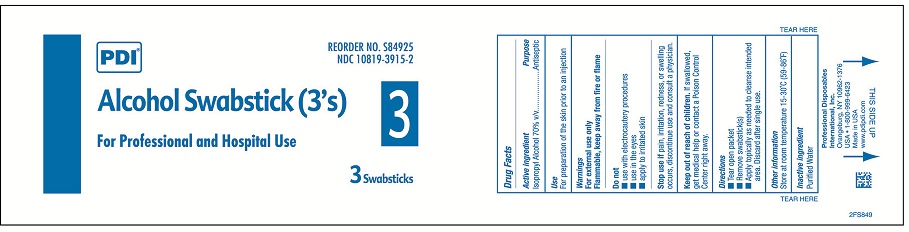 DRUG LABEL: PDI Alcohol Swabstick
NDC: 10819-3915 | Form: STICK
Manufacturer: Professional Disposables International, Inc.
Category: otc | Type: HUMAN OTC DRUG LABEL
Date: 20120127

ACTIVE INGREDIENTS: Alcohol 0.70 mL/1 mL
INACTIVE INGREDIENTS: Water

DRUG FACTS

Active Ingredient

Isopropyl Alcohol 70% v/v

Purpose

Antiseptic

Use

For preparation of the skin prior to an injection

Warnings

For external use only.
Flammable, keep away from fire or flame.
___________________________________________________
Do not

- use with electrocautery procedures
- use in the eyes
- apply to irritated skin

___________________________________________________
Stop use if pain, irritation, redness, or swelling occurs, discontinue use and consult a physician.

Keep out of reach of children. If swallowed, get medical help or contact a Poison Control Center right away.

Directions

- Tear open packet
- Remove awabstick(s)
- Apply topically as needed to cleanse intended area. Discard after single use.

Other Information

Store at room temperature 15-30oC (59-86oF)

Inactive ingredient

Purified water

Principal Display Panel

PDI(R)

Alcohol Swabstick (3's) and (1's)
For Professional and Hospital Use
Professional Disposables International, Inc.
Orangeburg, NY 10962-1376
USA - 1800-999-6423
www.pdipdi.com Made in USA
1 Swabstick
50 Packets [1 Swabstick per Packet]
3 Swabsicks

25 Packets [3 Swabsticks per Packet]

Packet Label Ones

Box Label Ones

Packet Label Threes

Box Label Threes

Dosage & Administration

Use one Swabstick at a time.